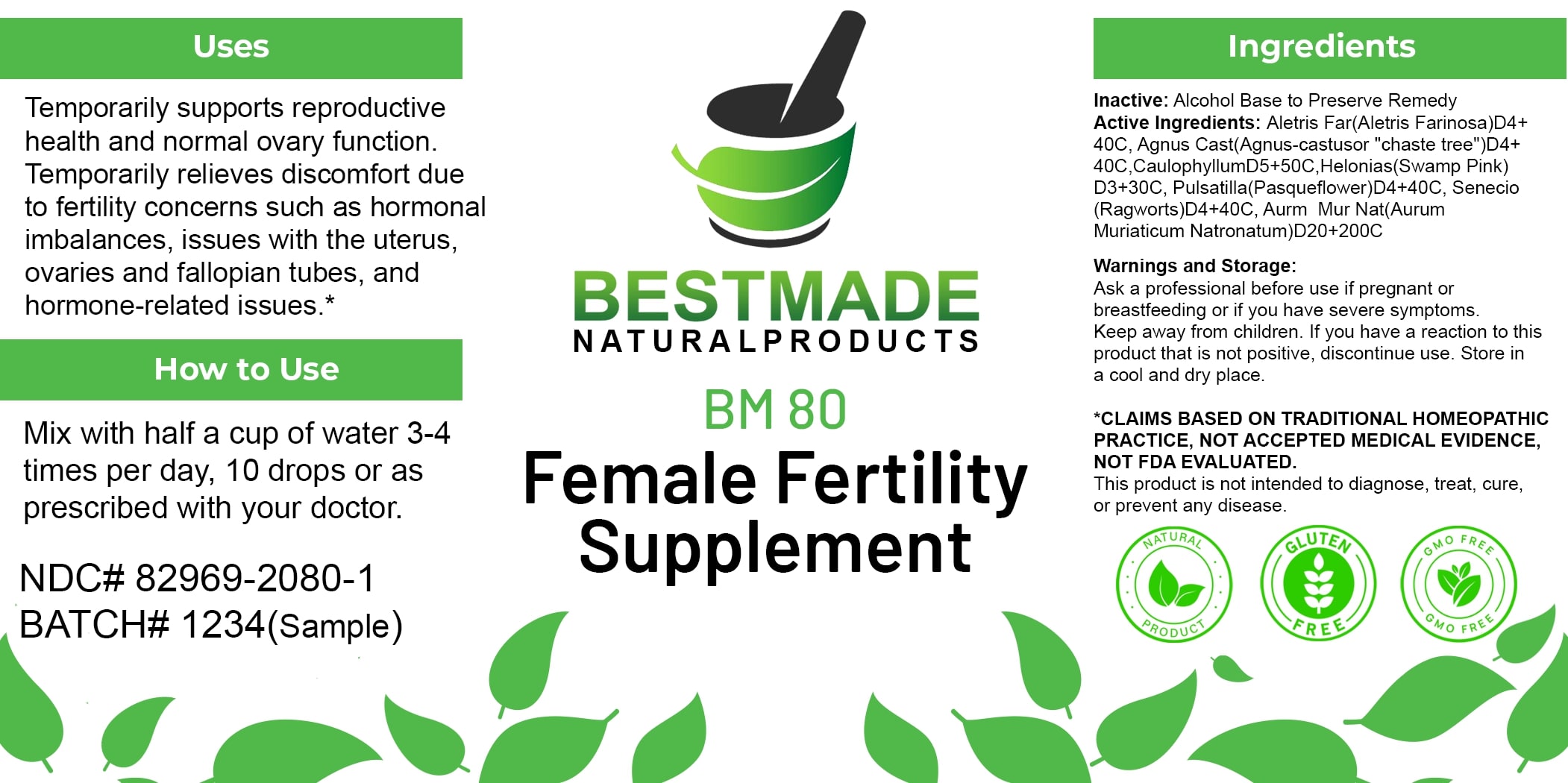 DRUG LABEL: Bestmade Natural Products BM80
NDC: 82969-2080 | Form: LIQUID
Manufacturer: Bestmade Natural Products
Category: homeopathic | Type: HUMAN OTC DRUG LABEL
Date: 20250131

ACTIVE INGREDIENTS: SODIUM TETRACHLOROAURATE 30 [hp_C]/30 [hp_C]; ALETRIS FARINOSA ROOT 30 [hp_C]/30 [hp_C]; CHASTE TREE 30 [hp_C]/30 [hp_C]; PACKERA AUREA 30 [hp_C]/30 [hp_C]; PULSATILLA PRATENSIS 30 [hp_C]/30 [hp_C]; CHAMAELIRIUM LUTEUM ROOT 30 [hp_C]/30 [hp_C]; CAULOPHYLLUM THALICTROIDES ROOT 30 [hp_C]/30 [hp_C]
INACTIVE INGREDIENTS: ALCOHOL 30 [hp_C]/30 [hp_C]

BM80

DOSAGE AND ADMINISTRATION

How to Use

Mix with half a cup of water 3-4 times per day, 10 drops or as prescribed with your doctor.

INACTIVE INGREDIENT

Ingredients

Inactive: Alcohol Base to Preserve Remedy

ACTIVE INGREDIENT

Active Ingredients: Aletris Far(Aletris Farinosa)D4+40C, Agnus Cast(Agnus-castuso "chaste tree")D4+40C, CaulophyllumD5+50C, Helonias(Swamp Pink) D3+30C, Pulsatilla(Pasqueflower)D4+40C, Senecio (Ragworts)D4+40C, Aurr. Mur Nat(Aurum Muriaticum Natronatum)D20+200C

Uses

Temporarily supports reproductive health and normal ovary function. Temporarily relieves discomfort due to fertility concerns such as hormonal imbalances, issues with the uterus, ovaries and fallopian tubes, and hormone-related issues.*

*CLAIMS BASED ON TRADITIONAL HOMEOPATHIC PRACTICE, NOT ACCEPTED MEDICAL EVIDENCE, NOT FDA EVALUATED.

This product is not intended to diagnose, treat, cure, or prevent any disease.

Uses

Temporarily supports reproductive health and normal ovary function. Temporarily relieves discomfort due to fertility concerns such as hormonal imbalances, issues with the uterus, ovaries and fallopian tubes, and hormone-related issues.*

*CLAIMS BASED ON TRADITIONAL HOMEOPATHIC PRACTICE, NOT ACCEPTED MEDICAL EVIDENCE, NOT FDA EVALUATED.

This product is not intended to diagnose, treat, cure, or prevent any disease.

KEEP OUT OF REACH OF CHILDREN

Warnings and Storage:

Ask a professional before use if pregnant or breastfeeding or if you have severe symptoms. Keep away from children. If you have a reaction to this product that is not positive, discontinue use. Store in a cool and dry place.

Warnings and Storage:

Ask a professional before use if pregnant or breastfeeding or if you have severe symptoms. Keep away from children. If you have a reaction to this product that is not positive, discontinue use. Store in a cool and dry place.

*CLAIMS BASED ON TRADITIONAL HOMEOPATHIC PRACTICE, NOT ACCEPTED MEDICAL EVIDENCE, NOT FDA EVALUATED.

This product is not intended to diagnose, treat, cure, or prevent any disease.

Entire package label